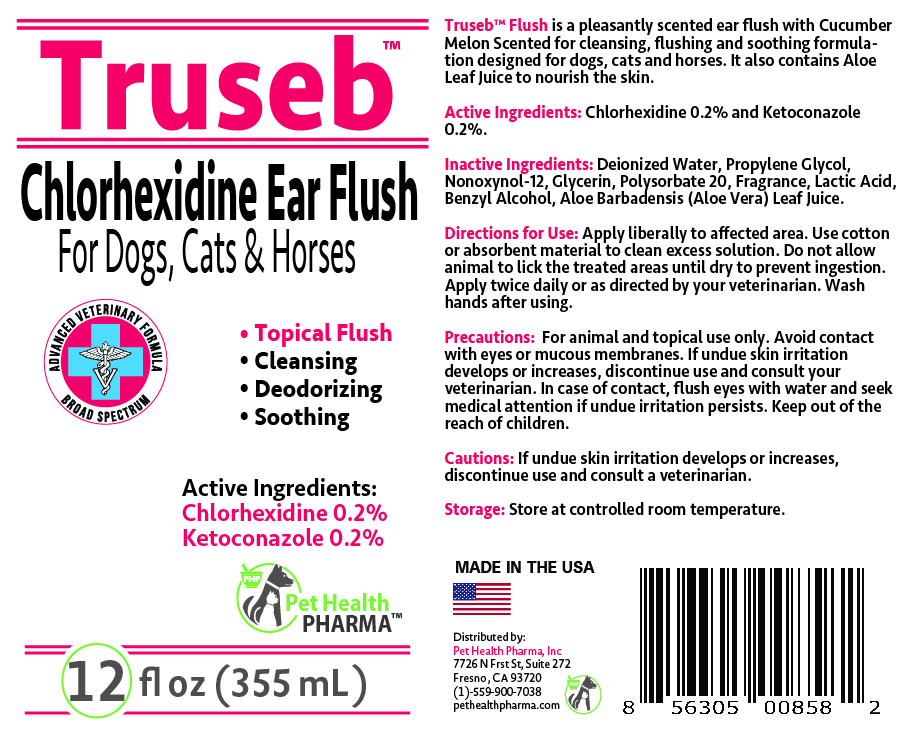 DRUG LABEL: Truseb Chlorhexidine for dogs, cats and Horses
NDC: 86176-202 | Form: SOLUTION
Manufacturer: Pet Health Pharma, LLC
Category: animal | Type: OTC ANIMAL DRUG LABEL
Date: 20250214

ACTIVE INGREDIENTS: CHLORHEXIDINE GLUCONATE 2 mg/1 mL; KETOCONAZOLE 2 mg/1 mL
INACTIVE INGREDIENTS: WATER; PROPYLENE GLYCOL; NONOXYNOL-12; GLYCERIN; POLYSORBATE 20; LACTIC ACID; BENZYL ALCOHOL; ALOE VERA LEAF

Truseb Chlorhexidine Gluconate, Ketoconazole Ear Flush for dogs, cats & Horses

ACTIVE INGREDIENTS:

Chlorhexidine Gluconate 0.2% and Ketoconazole 0.2%

INACTIVE INGREDIENT:

Water, Propylene Glycol USP, Nonoxynol-12, Glycerin, Polysorbate 20, Lactic Acid, Aloe Barbadensis (Aloe Vera) Leaf Juice, Fragrance, Benzyl Alcohol.

INDICATIONS & USAGE:

Truseb™ Flush is a pleasantly scented ear flush with Cucumber Melon Scented for cleansing, flushing and soothing formulation designed for dogs, cats and horses. It also contains Aloe Leaf Juice to nourish the skin

DOSAGE & ADMINISTRATION:

Apply liberally to affected area. Use cotton or absorbent material to clean excess solution. Do not allow animal to lick the treated areas until dry to prevent ingestion. Apply twice daily or as directed by your veterinarian. Wash hands after using.

PRECAUTIONS:

For animal and topical use only. Avoid contact with eyes or mucous membranes. If undue skin irritation develops or increases, discontinue use and consult your veterinarian. In case of contact, flush eyes with water and seek medical attention if undue irritation persists. Keep out of the reach of children.

STORAGE AND HANDLING:

Store at controlled room temperature.

CAUTIONS:

If undue skin irritation develops or increases, discontinue use and consult a veterinarian.

SPL UNCLASSIFIED SECTION:

Chlorhexidine Ear Flush

For Dogs, Cats & Horses

ADVANCED VETERINARY FORMULA
Broad Spectrum

• Topical Flush
• Cleansing
• Deodorizing
• Soothing

MADE IN USA

Distributed by:
Pet Health Pharma, Inc
7726 N Frst St, Suite 272
Fresno , CA 93720
(1)-559-900-7038
pethealthpharma.com

PACKAGE LABEL

Packaging

Add image transcription here...